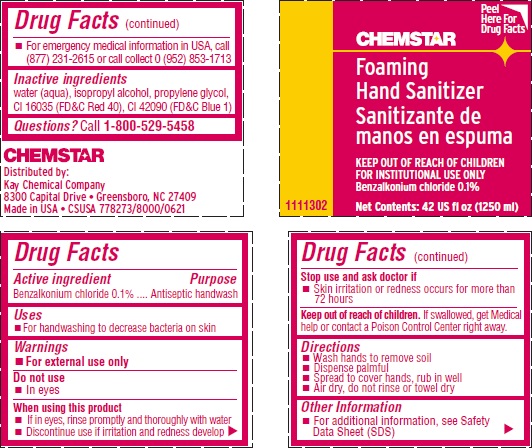 DRUG LABEL: CHEMSTAR Foaming Hand Sanitizer
NDC: 47593-689 | Form: SOLUTION
Manufacturer: Ecolab Inc.
Category: otc | Type: HUMAN OTC DRUG LABEL
Date: 20251218

ACTIVE INGREDIENTS: BENZALKONIUM CHLORIDE 0.1 mg/100 mL
INACTIVE INGREDIENTS: WATER; ISOPROPYL ALCOHOL; PROPYLENE GLYCOL; FD&C RED NO. 40; FD&C BLUE NO. 1

Drug Facts

Active ingredient

Benzalkonium chloride 0.1%

Purpose

Antiseptic handwash

INDICATIONS AND USAGE

- for handwashing to decrease bacteria on skin

Warnings

For external use only

Do not use

- in eyes

When using this product

- if in eyes, rinse promptly and throughly with water
- discontinue use if irritation and redness develop

Stop use and ask doctor if

- skin irritation or redness persists for more than 72 hours

Keep out of reach of children. If swallowed, get medical help or contact a Poison Control Center right away.

Directions

- wash hands to remove soil
- dispense palmful
- spread to cover hands, rub in well
- air dry, do not rinse or towel dry

Other Information

- For additional information, see Safety Data Sheet (SDS)
- For emergency medical information in USA, call (877) 231-2615 or call collect 0 (952) 853-1713

INACTIVE INGREDIENT

Inactive ingredients water (aqua), isopropyl alcohol, propylene glycol, CI 16035 (FD&C Red 40), CI 42090 (FD&C Blue 1)

Questions? call 1-800-529-5458

Principal Display Panel and Representative label

CHEMSTAR

Foaming

Hand Sanitizer

Sanitizante de manos en espuma

KEEP OUT OF REACH OF CHILDREN

FOR INSTITUTIONAL USE ONLY

Benzalkonium chloride 0.1%

Net Contents: 42 US fl oz (1250 ml)

1111302

Distributed by:

Kay Chemical Company

8300 Capital Drive • Greensboro, NC 27409

Made in USA • CSUSA 778273/8000/0621